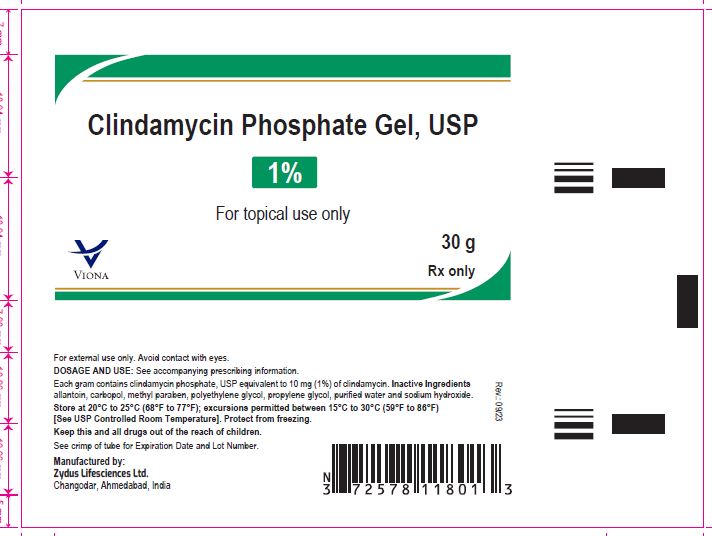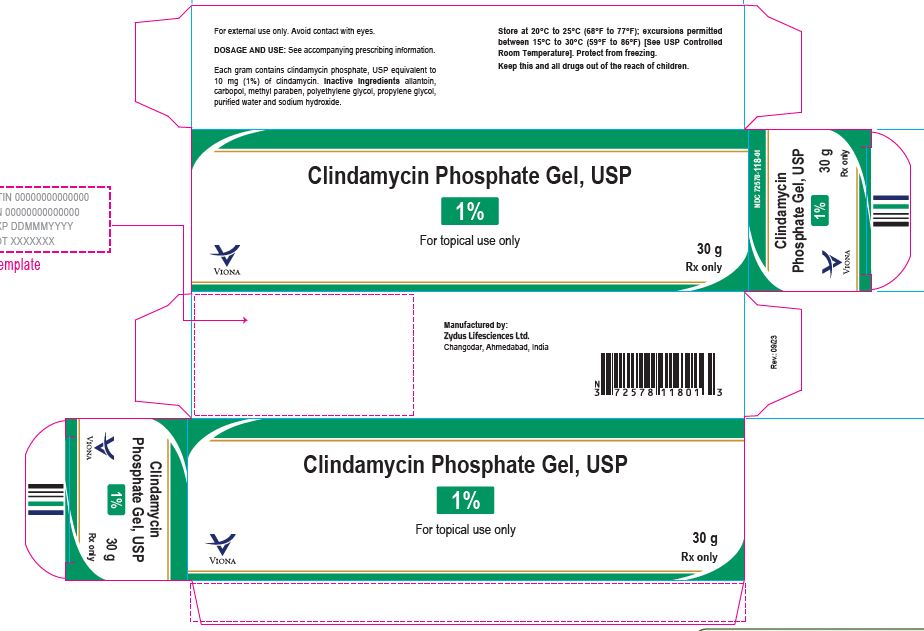 DRUG LABEL: Clindamycin Phosphate
NDC: 70771-1855 | Form: GEL
Manufacturer: Zydus Lifesciences Limited
Category: prescription | Type: HUMAN PRESCRIPTION DRUG LABEL
Date: 20230920

ACTIVE INGREDIENTS: CLINDAMYCIN PHOSPHATE 10 mg/1 g
INACTIVE INGREDIENTS: ALLANTOIN; CARBOMER HOMOPOLYMER TYPE B (ALLYL PENTAERYTHRITOL CROSSLINKED); METHYLPARABEN; POLYETHYLENE GLYCOL 400; PROPYLENE GLYCOL; SODIUM HYDROXIDE; WATER

Clindamycin Phosphate Gel USP, 1%

PACKAGE LABEL.PRINCIPAL DISPLAY PANEL

Clindamycin Phosphate Gel USP, 1%

30 g

NDC 70771-1855-2

Rx only